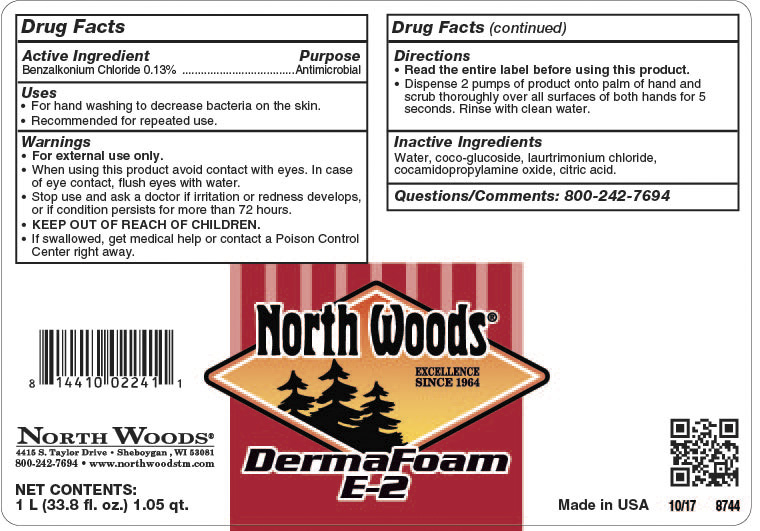 DRUG LABEL: North Woods Derma Foam E-2
NDC: 53125-817 | Form: SOAP
Manufacturer: Superior Chemical Corporation
Category: otc | Type: HUMAN OTC DRUG LABEL
Date: 20241118

ACTIVE INGREDIENTS: BENZALKONIUM CHLORIDE 1.3 mg/1 mL
INACTIVE INGREDIENTS: GLYCERIN; SODIUM BENZOATE; ALCOHOL; TETRASODIUM EDTA; WATER; LAURTRIMONIUM CHLORIDE; CAPRYLYL/CAPRYL OLIGOGLUCOSIDE; ANHYDROUS CITRIC ACID

North Woods Derma Foam E-2

Active Ingredient

Benzalkonium Chloride 0.13%

Uses

- For handwashing to decrease the bacteria on the skin.
- Recommended for repeated use.

Warnings

- For external use only.
- When using this product avoid contact with eyes. In case of eye contact, flush eyes with water.
- Stop use and ask a doctor If irritation persists or redness deelops, or if condition persists for more than 72 hours.
- Keep out of reach of children.
- If swallowed, get medical help or contact a Poison Control Center right away.

Directions

- Read the entire label before using this product.
- Dispense 2 pumps of product onto palm of hand and scrub thoroughly over all surfaces of both hands for 15 seconds. Rinse with clean water.

Inactive Ingredients

Water, coco-glucoside, laurtrimonium chloride, cocamidopropylamine oxide, citric acid.

Superior Derma Foam E2

Purpose

Antimicrobial

Superior Derma Foam E2

KEEP OUT OF REACH OF CHILDREN

Superior Derma Foam E2

71729-00 Superior Derma Foam E2